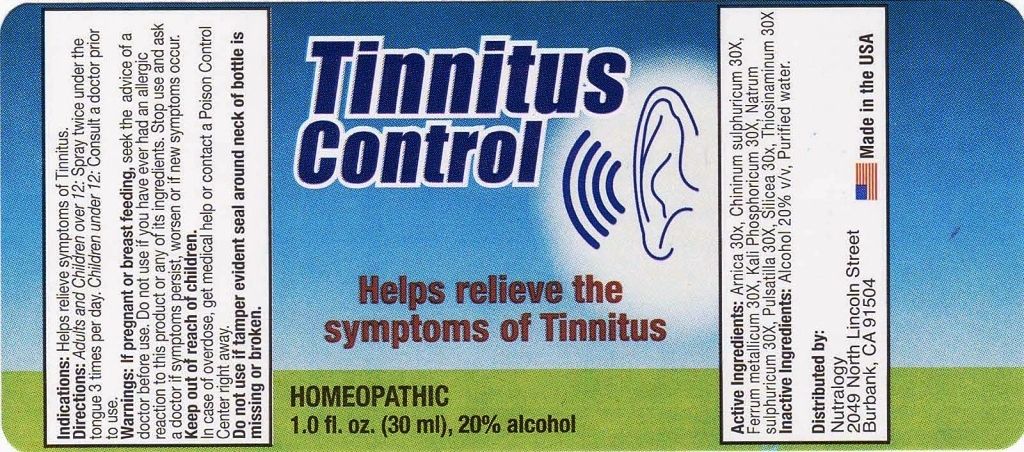 DRUG LABEL: Tinnitus Control
NDC: 50845-0130 | Form: SPRAY
Manufacturer: Liddell Laboratories, Inc.
Category: homeopathic | Type: HUMAN OTC DRUG LABEL
Date: 20110426

ACTIVE INGREDIENTS: ARNICA MONTANA 30 [hp_X]/1 mL; QUININE SULFATE 30 [hp_X]/1 mL; IRON 30 [hp_X]/1 mL; POTASSIUM PHOSPHATE, DIBASIC 30 [hp_X]/1 mL; SODIUM SULFATE 30 [hp_X]/1 mL; PULSATILLA VULGARIS 30 [hp_X]/1 mL; SILICON DIOXIDE 30 [hp_X]/1 mL; ALLYLTHIOUREA 30 [hp_X]/1 mL
INACTIVE INGREDIENTS: WATER; ALCOHOL

Tinnitus Control

ACTIVE INGREDIENT

ACTIVE INGREDIENTS: Arnica montana 30X, Chininum sulphuricum 30X, Ferrum Metallicum 30X, Kali phosphoricum 30X, Natrum sulphuricum 30X, Pulsatilla 30X, Silicea 30X, Thiosinaminum 30X.

PURPOSE

INDICATIONS: Helps relieve symptoms of Tinnitus.

WARNINGS

WARNINGS: If pregnant or breast feeding, seek the advice of a doctor before use.

Do not use if you have ever had an allergic reaction to this product or any of its ingredients.

Stop use and ask a doctor if symptoms persist, worsen or if new symptoms occur.

Keep out of reach of children. In case of overdose, get medical help or contact a Poison Control Center right away.

Do not use if tamper evident seal around neck of bottle is missing or broken.

DOSAGE AND ADMINISTRATION

DIRECTIONS: Adults and Children over 12: Spray twice under the tongue 3 times per day. Children under 12: Consult a doctor prior to use.

INACTIVE INGREDIENTS: Alcohol 20% v/v, Purified water.

INDICATIONS: Helps relieve symptoms of Tinnitus.

QUESTIONS

Distributed by:

Nutralogy

2049 North Lincoln Street

Burbank, CA 91504

Made in the USA

KEEP OUT OF REACH OF CHILDREN. In case of overdose, get medical help or contact a Poison Control Center right away.

PACKAGE LABEL

Tinnitus Control

Helps relieve the symptoms of Tinnitus

HOMEOPATHIC

1.0 fl. oz. (30 ml)